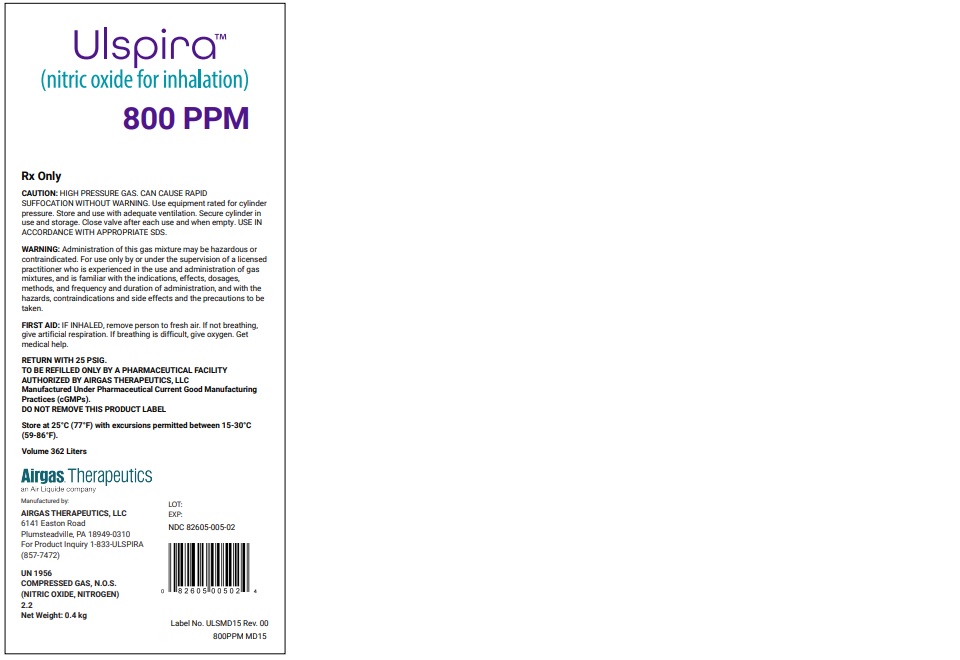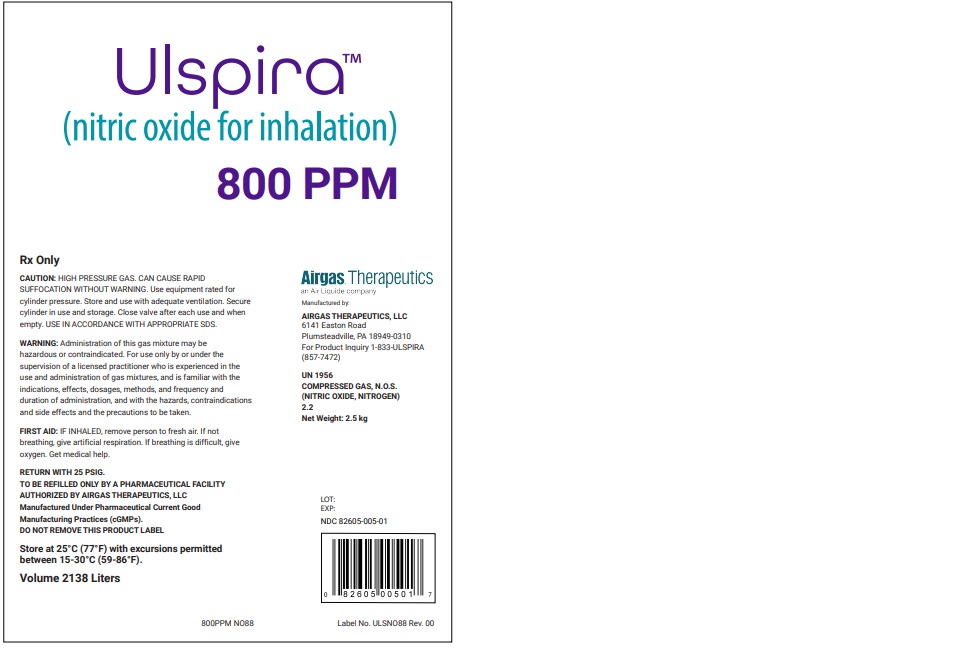 DRUG LABEL: Ulspira
NDC: 82605-008 | Form: GAS
Manufacturer: Airgas Therapeutics, LLC
Category: prescription | Type: HUMAN PRESCRIPTION DRUG LABEL
Date: 20251030

ACTIVE INGREDIENTS: NITRIC OXIDE 0.8 mL/100 L
INACTIVE INGREDIENTS: NITROGEN 999.2 mL/100 L

Nitric Oxide 800 PPM

WARNINGS

WARNING: Administration of this gas mixture may be hazardous or contraindicated. For use only by or under the supervision of a licensed practitioner who is experienced in the use and administration of gas mixtures, and if familiar with the indications, effects, dosages, methods, and frequency and duration of administration, and with the hazards, contraindications and side effects and the precautions to be taken.

PACKAGE LABEL

Ulspira TM

(nitric oxide for inhalation)

800 PPM

Rx Only

CAUTION: HIGH PRESSURE GAS. CAN CAUSE RAPID SUFFOCATION WITHOUT WARNING. Use equipment rated for cylinder pressure. Store and use with adequate ventilation. Secure cylinder in use and storage. Close valve after each use and when empty. USE IN ACCORDANCE WITH APPROPRIATE SDS.

WARNING: Administration of this gas mixture may be hazardous or contraindicated. For use only by or under the supervision of a licensed practitioner who is experienced in the use and administration of gas mixtures, and if familiar with the indications, effects, dosages, methods, and frequency and duration of administration, and with the hazards, contraindications and side effects and the precautions to be taken.

FIRST AID: IF INHALED, remove person to fresh air. If not breathing, give artificial respiration. If breathing is difficult, give oxygen. Get medical help.

RETURN WITH 25 PSIG.

TO BE REFILLED ONLY BY A PHARMACEUTICAL FACILITY

AUTHORIZED BY AIRGAS THERAPEUTICS, LLC

Manufactured Under Pharmaceutical Current Good Manufacturing Practices (cGMPs).

DO NOT REMOVE THIS PRODUCT LABELS

Store at 25 C (77 F) with excursions permitted between 15 - 30 C (59 – 86 F).

Volume 362 Liters

Airgas Therapeutics

An Air Liquide company

Manufactured by:

AIRGAS THERAPEUTICS, LLC

6141

Easton Road

Plumsteadville, PA 18949-0310

For Product Inquiry 1-833-ULSPIRA (857-7472)

UN 1956

COMPRESSED GAS, N.O.S. (NITRIC OXIDE, NITROGEN) 2.2

Net Weight: 0.4 kg

LOT:

EXP:

NDC 82605-005-02

Label No. ULSMD15 Rev. 00

800PPM MD15

PACKAGE LABEL

Ulspira TM

(nitric oxide for inhalation)

800 PPM

Rx Only

CAUTION: HIGH PRESSURE GAS. CAN CAUSE RAPID SUFFOCATION WITHOUT WARNING. Use equipment rated for cylinder pressure. Store and use with adequate ventilation. Secure cylinder in use and storage. Close valve after each use and when empty. USE IN ACCORDANCE WITH APPROPRIATE SDS.

WARNING: Administration of this gas mixture may be hazardous or contraindicated. For use only by or under the supervision of a licensed practitioner who is experienced in the use and administration of gas mixtures, and is familiar with the indications, effects, dosages, methods, and frequency and duration of administration, and with the hazards, contraindications, and side effects and the precautions to be taken.

FIRST AID: IF INHALED, remove person to fresh air. If not breathing, give artificial respiration. If breathing is difficult, give oxygen. Get medical help.

RETURN WITH 25 PSIG.

TO BE REFILLED ONLY BY A PHARMACEUTICAL FACILITY

AUTHORIZED BY AIRGAS THERAPEUTICS, LLC

Manufactured Under Pharmaceutical Current Good Manufacturing Practices (cGmps).

DO NOT REMOVE THIS PRODUCT LABEL

Store at 25 C (77 F) with excursions permitted between 15 – 30 C (59 – 86 F).

Volume 2138 Liters

Airgas Therapeutics

An Air Liquide company

Manufactured by:

AIRGAS THERAPEUTICS, LLC

6141 Easton Road

Plumsteadville, PA 18949-0310

For Product Inquiry 1-833-ULSPIRA (857-7472)

UN1956

COMPRESSED GAS, N.O.S. (NITRIC OXIDE, NITROGEN) 2.2

Net Weight: 2.5 kg

LOT:

EXP:

NDC 82605-005-01